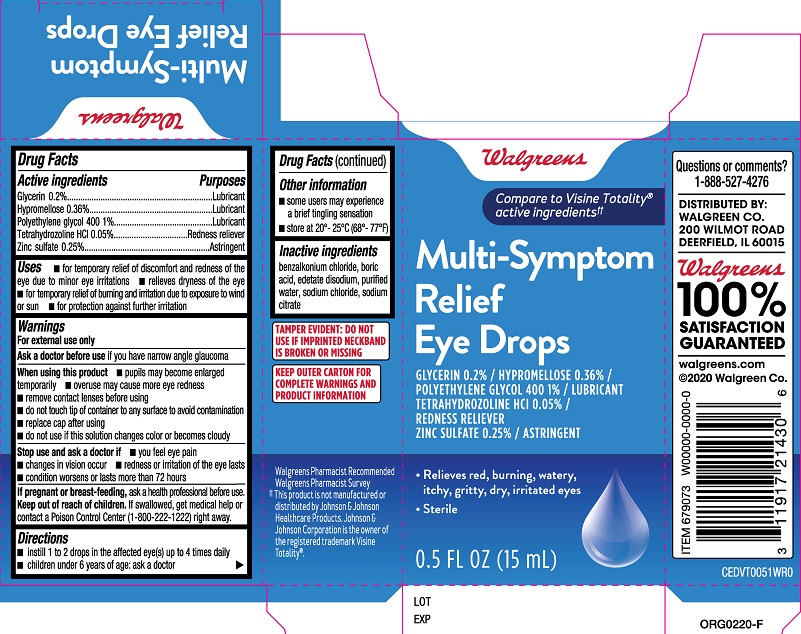 DRUG LABEL: Walgreens Multi-Symptom Relief Eye Drops
NDC: 0363-1462 | Form: SOLUTION/ DROPS
Manufacturer: Walgreen Co.
Category: otc | Type: HUMAN OTC DRUG LABEL
Date: 20231220

ACTIVE INGREDIENTS: HYPROMELLOSE, UNSPECIFIED 0.36 g/100 mL; POLYETHYLENE GLYCOL 400 1 g/100 mL; ZINC SULFATE 0.25 g/100 mL; GLYCERIN 0.2 g/100 mL; TETRAHYDROZOLINE HYDROCHLORIDE 0.05 g/100 mL
INACTIVE INGREDIENTS: BENZALKONIUM CHLORIDE; SODIUM CHLORIDE; SODIUM CITRATE; BORIC ACID; EDETATE DISODIUM; WATER

Walgreens Multi-Symptom Relief Eye Drops (PLD)

Active ingredients

Glycerin ....0.2%

Hypromellose.....0.36%

Polyethylene glycol 400.....1%

Tetrahydrozoline HCl.....0.05%

Zinc sulfate 0.25%

Purposes

Glycerin ....Lubricant

Hypromellose.....Lubricant

Polyethylene glycol 400.....Lubricant

Tetrahydrozoline HCl.....Redness reliever

Zinc sulfate.....Astringent

Uses

- for temporary relief of discomfort and redness of the eye due to minor eye irritations
- relieves dryness of the eye
- for temporary relief of burning and irritation due to exposure to wind or sun
- for protection against further irritation

Uses

- for temporary relief of discomfort and redness of the eye due to minor eye irritations
- relieves dryness of the eye
- for temporary relief of burning and irritation due to exposure to wind or sun
- for protection against further irritation

Warnings

For external use only

Ask a doctor before use if you have narrow angle glaucoma

When using this product

- pupils may become enlarged temporarily
- overuse may cause more eye redness
- remove contact lenses before using
- do not touch tip of container to any surface to avoid contamination
- replace cap after using
- do not use if this solution changes color or becomes cloudy

Stop use and ask a doctor if

- you feel eye pain
- changes in vision occur
- redness or irritation of the eye lasts
- condition worsens or lasts more than 72 hours

PREGNANCY OR BREAST FEEDING

If pregnant or breast-feeding, ask a health professional before use.

Keep out of reach of children. If swallowed, get medical help or contact a Poison Control Center (1-800-222-1222) right away.

Directions

- instill 1 to 2 drops in the affected eye(s) up to 4 times daily
- children under 6 years of age: ask a doctor

Other information

- some users may experience a brief tingling sensation
- store at 20º-25ºC (68º-77ºF)

Inactive ingredients

- benzalkonium chloride, boric acid, edetate disodium, purified water, sodium chloride, sodium citrate

Questions or comments?

1-888-527-4276